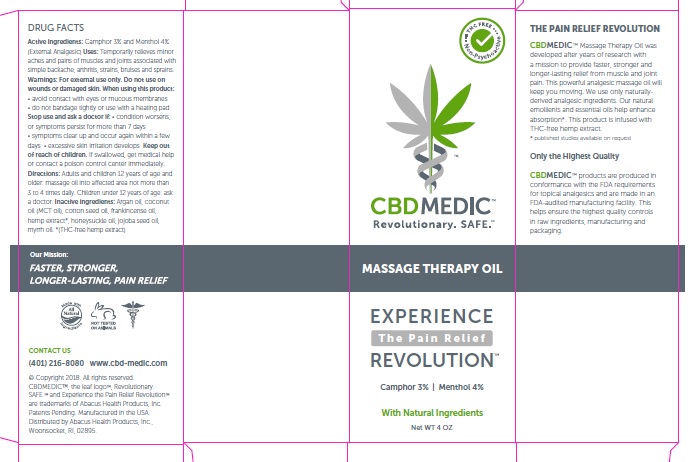 DRUG LABEL: CBDMEDIC MASSAGE THERAPY
NDC: 24909-727 | Form: OIL
Manufacturer: AIDANCE SKINCARE & TOPICAL SOLUTIONS, LLC
Category: otc | Type: HUMAN OTC DRUG LABEL
Date: 20181117

ACTIVE INGREDIENTS: CAMPHOR (SYNTHETIC) 30 g/1 mL; MENTHOL 40 g/1 mL
INACTIVE INGREDIENTS: ARGAN OIL; COCONUT OIL; COTTONSEED OIL; FRANKINCENSE OIL; HEMP; LONICERA CONFUSA WHOLE; JOJOBA OIL; MYRRH OIL

CBDMEDIC Massage Therapy Oil

Active Ingredients and Purpose

Camphor 3%, Menthol 4% (External Analgesics)

Uses

Temporarily relieves minor aches and pains of muscles and joints associated with simple backache, arthritis, strains, bruises and sprains.

Warnings

For external use only. Do not use on wounds or damaged skin. When using this product: • avoid contact with eyes or mucous membranes • do not bandage tightly or use with a heating pad. Stop use and ask a doctor if: • condition worsens, or symptoms persist for more than 7 days • symptoms clear up and occur again within a few days • excessive skin irritation develops.

Keep out of reach of children

If swallowed, get medical help or contact a poison control center immediately.

Directions

Adults and children 12 years of age and older: massage oil into affected area not more than 3 to 4 times daily. Children under 12 years of age: ask a doctor.

Inactive ingredients

Argan oil, Coconut Oil (MCT oil), Cotton seed Oil, Frankincense Oil, Hemp extract*, Honeysuckle Oil, Jojoba seed oil, Myrrh Oil. *(THC-free hemp extract)